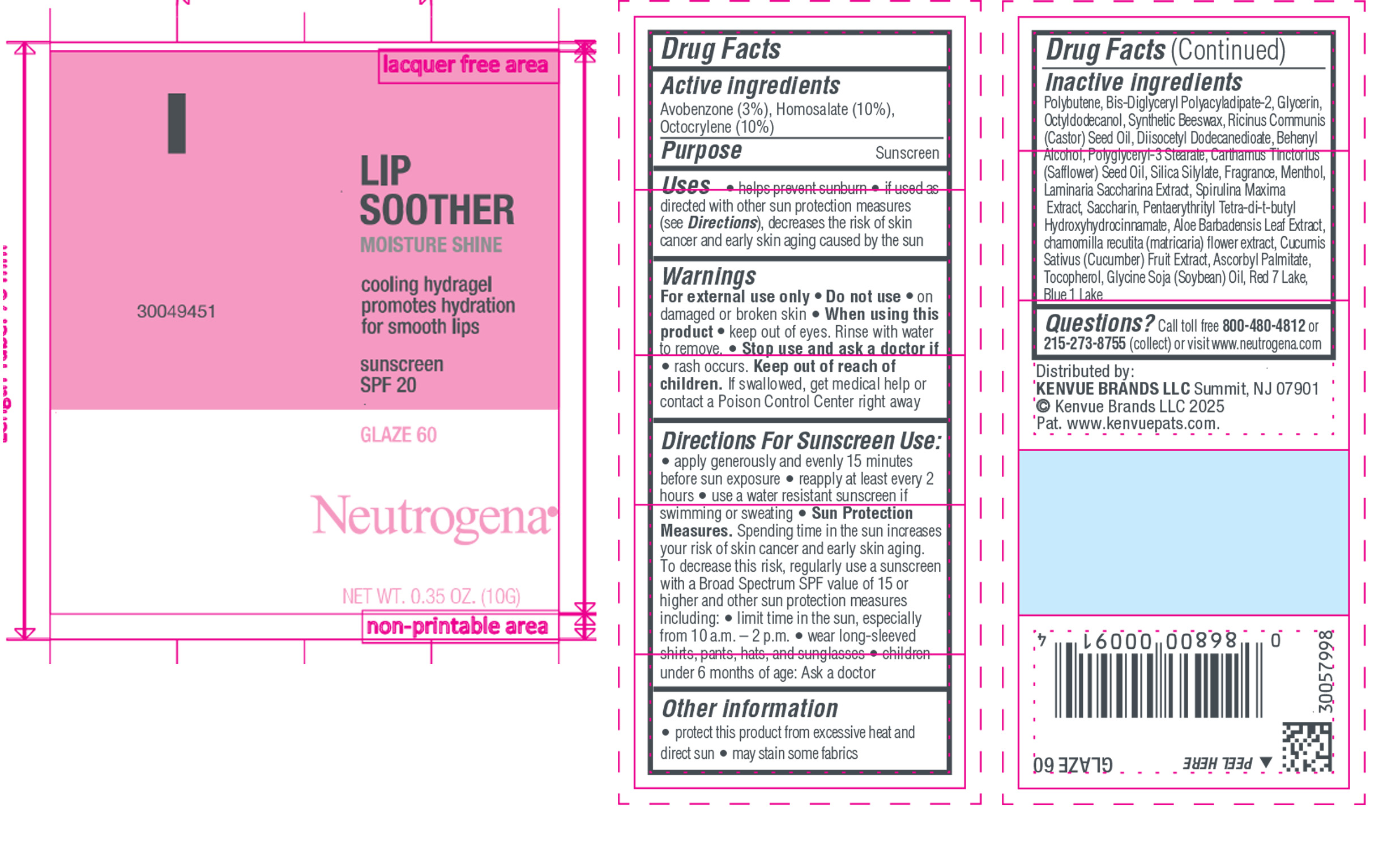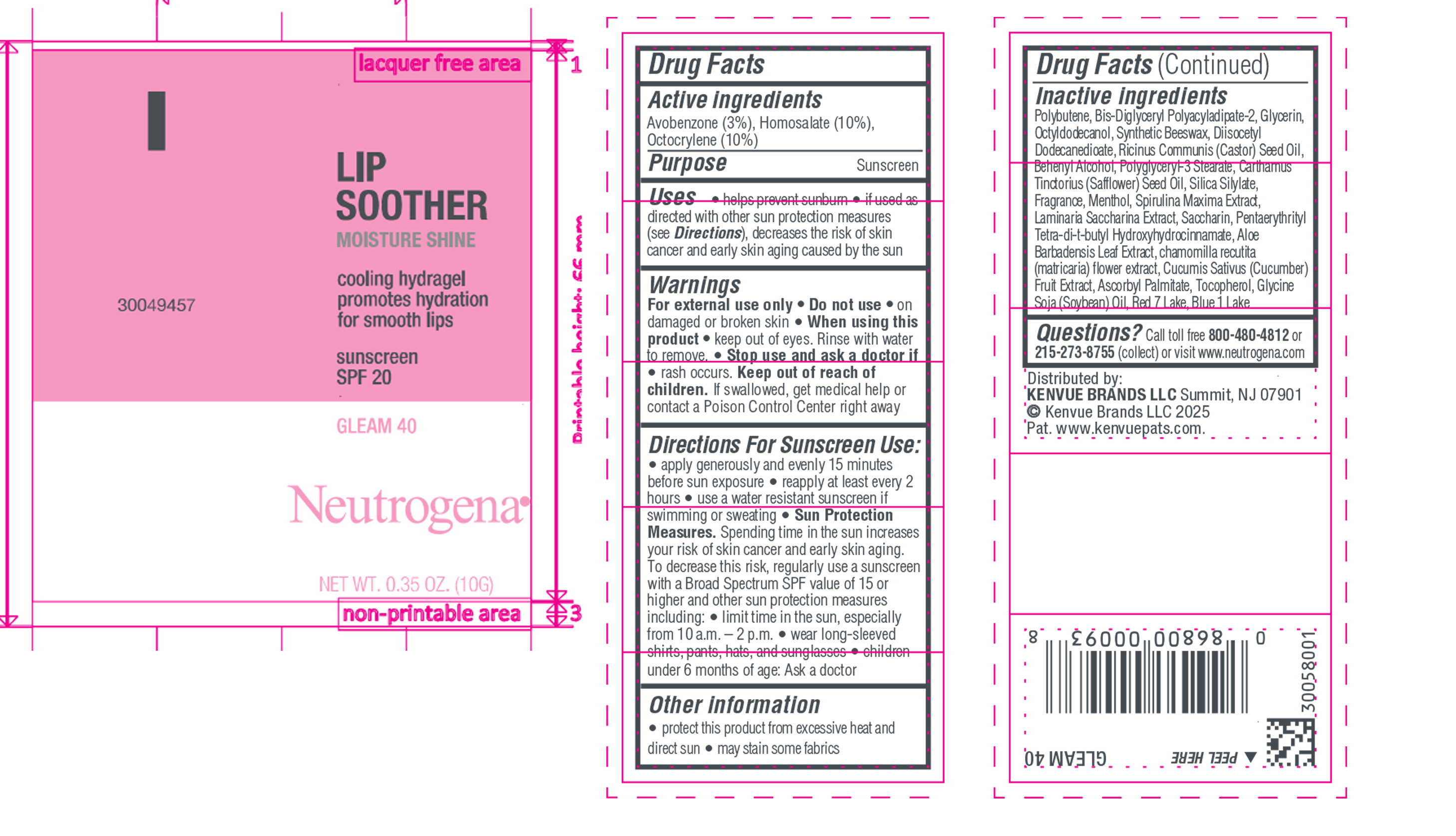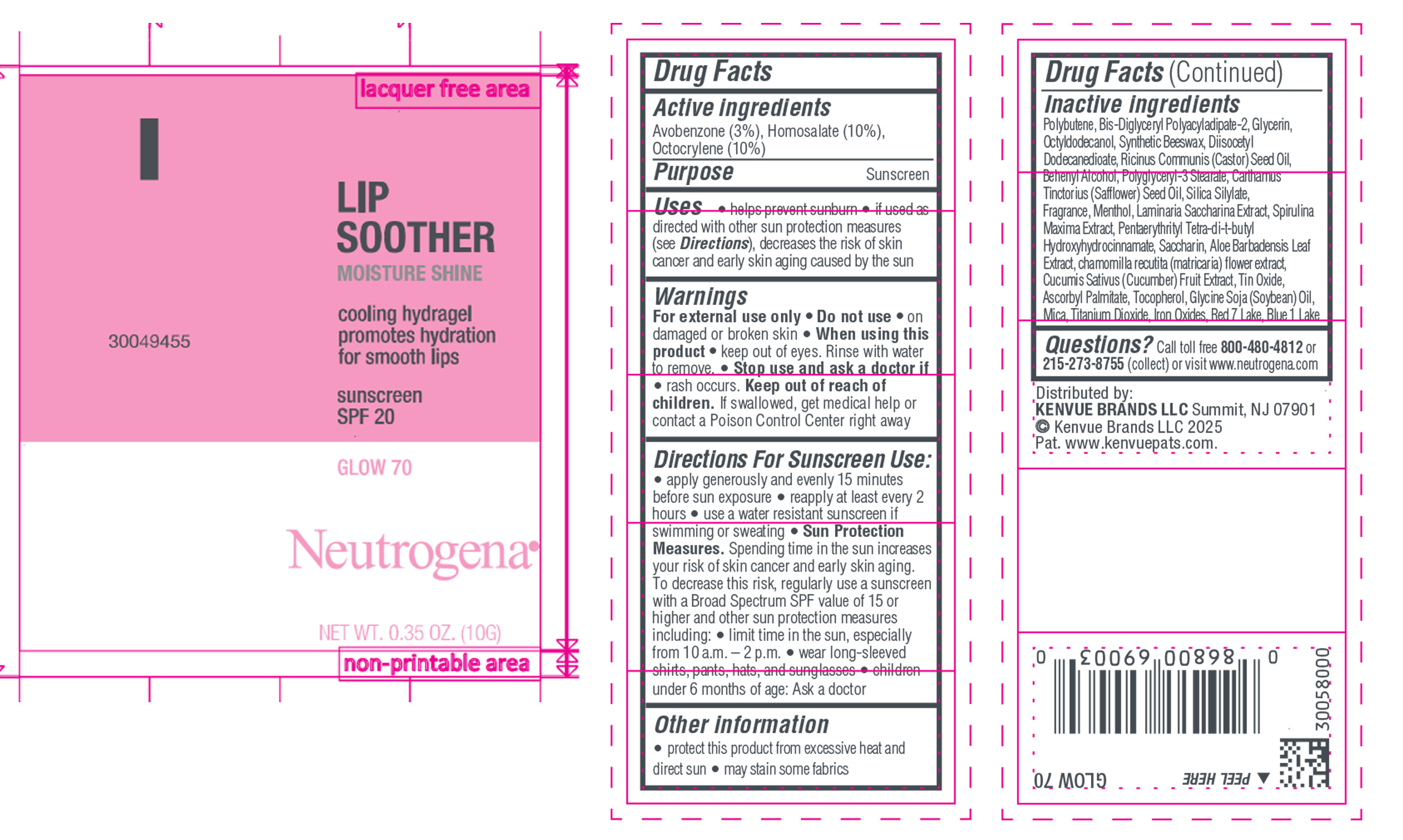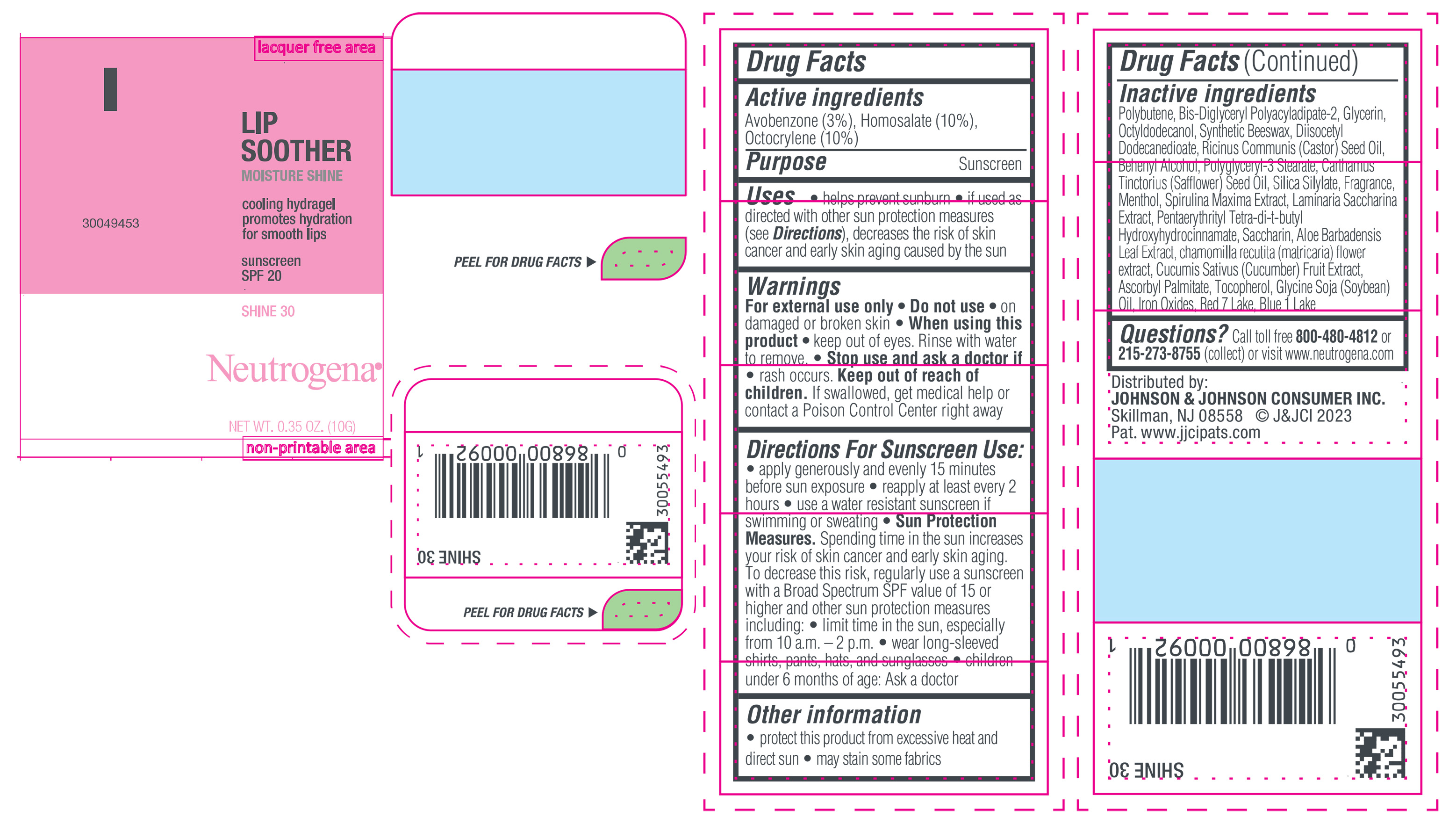 DRUG LABEL: Neutrogena MoistureShine Lip Soother with Sunscreen SPF 20, Shine 30
NDC: 69968-0849 | Form: GEL
Manufacturer: Kenvue Brands LLC
Category: otc | Type: HUMAN OTC DRUG LABEL
Date: 20250210

ACTIVE INGREDIENTS: HOMOSALATE 100 mg/1 g; OCTOCRYLENE 100 mg/1 g; AVOBENZONE 30 mg/1 g
INACTIVE INGREDIENTS: GLYCERIN; DIISOCETYL DODECANEDIOATE; CASTOR OIL; POLYGLYCERYL-3 STEARATE; TOCOPHEROL; D&C RED NO. 7; OCTYLDODECANOL; POLYBUTENE (1400 MW); FERROUS OXIDE; BIS-DIGLYCERYL POLYACYLADIPATE-2; DOCOSANOL; SAFFLOWER OIL; MENTHOL; ALOE VERA LEAF; CHAMOMILE; SYNTHETIC BEESWAX; CUCUMBER; SACCHARINA LATISSIMA; SPIRULINA MAXIMA; SACCHARIN; ASCORBYL PALMITATE; PENTAERYTHRITOL TETRAKIS(3-(3,5-DI-TERT-BUTYL-4-HYDROXYPHENYL)PROPIONATE); SOYBEAN OIL; FD&C BLUE NO. 1 ALUMINUM LAKE

Neutrogena MoistureShine Lip Soother with Sunscreen SPF 20, Shine 30
Neutrogena MoistureShine Lip Soother with Sunscreen SPF 20, Gleam 40
Neutrogena MoistureShine Lip Soother with Sunscreen SPF 20, Glaze 60
Neutrogena MoistureShine Lip Soother with Sunscreen SPF 20, Glow 70

Drug Facts

Active ingredient

Avobenzone (3%), Homosalate (10%), Octocrylene (10%)

Purpose

Sunscreen

Use

• helps prevent sunburn

• if used as directed with other sun protection measures (see Directions), decreases the risk of skin cancer and early skin aging caused by the sun

Warnings

For external use only.

Do not use

on damaged or broken skin

When using this product

keep out of eyes. Rinse with water to remove.

Stop use and ask a doctor if

rash occurs.

Keep out of reach of children

If swallowed, get medical help or contact a Poison Control Center right away

Directions For Sunscreen Use

• apply generously and evenly 15 minutes before sun exposure

• reapply at least every 2 hours

• use a water resistant sunscreen if swimming or sweating

• Sun Protection Measures. Spending time in the sun increases your risk of skin cancer and early skin aging. To decrease this risk, regularly use a sunscreen with a Broad Spectrum SPF value of 15 or higher and other sun protection measures including:

• limit time in the sun, especially from 10 a.m. – 2 p.m.

• wear long-sleeved shirts, pants, hats, and sunglasses

• children under 6 months of age: Ask a doctor

Other Information

• protect this product from excessive heat and direct sun

• may stain some fabrics

Inactive ingredients

Polybutene, Bis-Diglyceryl Polyacyladipate-2, Glycerin, Octyldodecanol, Synthetic Beeswax, Diisocetyl Dodecanedioate, Ricinus Communis (Castor) Seed Oil, Behenyl Alcohol, Polyglyceryl-3 Stearate, Carthamus Tinctorius (Safflower) Seed Oil, Silica Silylate, Fragrance, Menthol, Spirulina Maxima Extract, Laminaria Saccharina, Extract, Pentaerythrityl Tetra-di-t-butyl Hydroxyhydrocinnamate, Saccharin, Aloe Barbadensis Leaf Extract, chamomilla recutita (matricaria) flower extract, Cucumis Sativus (Cucumber) Fruit Extract, Ascorbyl Palmitate, Tocopherol, Glycine Soja (Soybean) Oil, Iron Oxides, Red 7 Lake, Blue 1 Lake

Questions?

Call toll free 800-480-4812 or 215-273-8755 (collect) or visit www.neutrogena.com

Distributed by:

JOHNSON & JOHNSON

CONSUMER INC.

Skillman, NJ 08558

Drug Facts

Active ingredients

Avobenzone (3%), Homosalate (10%), Octocrylene (10%)

Purpose

Sunscreen

Use

• helps prevent sunburn

• if used as directed with other sun protection measures (see Directions), decreases the risk of skin cancer and early skin aging caused by the sun

Warnings

For external use only

Do not use

on damaged or broken skin

When using this product

keep out of eyes. Rinse with water to remove.

Stop use and ask a doctor if

rash occurs.

Keep out of reach of children

If swallowed, get medical help or contact a Poison Control Center right away

Directions For Sunscreen Use

• apply generously and evenly 15 minutes before sun exposure

• reapply at least every 2 hours

• use a water resistant sunscreen if swimming or sweating

• Sun Protection Measures. Spending time in the sun increases your risk of skin cancer and early skin aging. To decrease this risk, regularly use a sunscreen with a Broad Spectrum SPF value of 15 or higher and other sun protection measures including:

• limit time in the sun, especially from 10 a.m. – 2 p.m.

• wear long-sleeved shirts, pants, hats, and sunglasses

• children under 6 months of age: Ask a doctor

Other information

• protect this product from excessive heat and direct sun

• may stain some fabrics

Inactive ingredients

Polybutene, Bis-Diglyceryl Polyacyladipate-2, Glycerin, Octyldodecanol, Synthetic Beeswax, Diisocetyl Dodecanedioate, Ricinus Communis (Castor) Seed Oil, Behenyl Alcohol, Polyglyceryl-3 Stearate, Carthamus Tinctorius (Safflower) Seed Oil, Silica Silylate, Fragrance, Menthol, Spirulina Maxima Extract, Laminaria Saccharina, Extract, Saccharin, Pentaerythrityl Tetra-di-t-butyl Hydroxyhydrocinnamate, Aloe Barbadensis Leaf Extract, chamomilla recutita (matricaria) flower extract, Cucumis Sativus (Cucumber) Fruit Extract, Ascorbyl Palmitate, Tocopherol, Glycine Soja (Soybean) Oil, Red 7 Lake, Blue 1 Lake

Questions?

Call toll free 800-480-4812 or 215-273-8755 (collect) or visit www.neutrogena.com

Distributed by:

Kenvue Brands LLC
Summit, NJ 07901

Drug Facts

Active ingredients

Avobenzone (3%), Homosalate (10%), Octocrylene (10%)

Purpose

Sunscreen

Use

• helps prevent sunburn

• if used as directed with other sun protection measures (see Directions), decreases the risk of skin cancer and early skin aging caused by the sun

Warnings

For external use only.

Do not use

on damaged or broken skin

When using this product

keep out of eyes. Rinse with water to remove.

Stop use and ask a doctor if

rash occurs.

Keep out of reach of children

If swallowed, get medical help or contact a Poison Control Center right away

Directions For Sunscreen Use

• apply generously and evenly 15 minutes before sun exposure

• reapply at least every 2 hours

• use a water resistant sunscreen if swimming or sweating

• Sun Protection Measures. Spending time in the sun increases your risk of skin cancer and early skin aging. To decrease this risk, regularly use a sunscreen with a Broad Spectrum SPF value of 15 or higher and other sun protection measures including:

• limit time in the sun, especially from 10 a.m. – 2 p.m.

• wear long-sleeved shirts, pants, hats, and sunglasses

• children under 6 months of age: Ask a doctor

Other information

• protect this product from excessive heat and direct sun

• may stain some fabrics

Inactive ingredients

Polybutene, Bis-Diglyceryl Polyacyladipate-2, Glycerin, Octyldodecanol, Synthetic Beeswax, Ricinus Communis (Castor) Seed Oil, Diisocetyl Dodecanedioate, , Behenyl Alcohol, Polyglyceryl-3 Stearate, Carthamus Tinctorius (Safflower) Seed Oil, Silica Silylate, Fragrance, Menthol, Laminaria Saccharina Extract, Spirulina Maxima Extract, , Saccharin , Pentaerythrityl Tetra-di-t-butyl Hydroxyhydrocinnamate, , Aloe Barbadensis Leaf Extract, chamomilla recutita (matricaria) flower extract, Cucumis Sativus (Cucumber) Fruit Extract, Ascorbyl Palmitate, Tocopherol, Glycine Soja (Soybean) Oil, Red 7 Lake, Blue 1 Lake

Questions?

Call toll free 800-480-4812 or 215-273-8755 (collect) or visit www.neutrogena.com

Distributed by:

Kenvue Brands LLC
Summit, NJ 07901

Drug Facts

Active ingredients

Avobenzone (3%), Homosalate (10%), Octocrylene (10%)

Purpose

Sunscreen

Use

• helps prevent sunburn

• if used as directed with other sun protection measures (see Directions), decreases the risk of skin cancer and early skin aging caused by the sun

Warnings

For external use only

Do not use

on damaged or broken skin

When using this product

keep out of eyes. Rinse with water to remove.

Stop use and ask a doctor if

rash occurs.

Keep out of reach of children

If swallowed, get medical help or contact a Poison Control Center right away

Directions For Sunscreen Use

• apply generously and evenly 15 minutes before sun exposure

• reapply at least every 2 hours

• use a water resistant sunscreen if swimming or sweating

• Sun Protection Measures. Spending time in the sun increases your risk of skin cancer and early skin aging. To decrease this risk, regularly use a sunscreen with a Broad Spectrum SPF value of 15 or higher and other sun protection measures including:

• limit time in the sun, especially from 10 a.m. – 2 p.m.

• wear long-sleeved shirts, pants, hats, and sunglasses

• children under 6 months of age: Ask a doctor

Other information

• protect this product from excessive heat and direct sun

• may stain some fabrics

Inactive ingredients

Polybutene, Bis-Diglyceryl Polyacyladipate-2, Glycerin, Octyldodecanol, Synthetic Beeswax, Diisocetyl Dodecanedioate, Ricinus Communis (Castor) Seed Oil, Behenyl Alcohol, Polyglyceryl-3 Stearate, Carthamus Tinctorius (Safflower) Seed Oil, Silica Silylate, Fragrance, Menthol, Laminaria Saccharina Extract, Spirulina Maxima Extract, Pentaerythrityl Tetra-di-t-butyl Hydroxyhydrocinnamate, Saccharin, Aloe Barbadensis Leaf Extract, chamomilla recutita (matricaria) flower extract, Cucumis Sativus (Cucumber) Fruit Extract, Tin Oxide, Ascorbyl Palmitate, Tocopherol, Glycine Soja (Soybean) Oil, Mica, Titanium Dioxide, Iron Oxides, Red 7 Lake, Blue 1 Lake

Questions?

Call toll free 800-480-4812 or 215-273-8755 (collect) or visit www.neutrogena.com

Distributed by:

Kenvue Brands LLC
Summit, NJ 07901

PRINCIPAL DISPLAY PANEL - 10 g Tube Label, Shine 30

LIP

SOOTHER

MOISTURE SHINE

cooling hydragel

promotes hydration

for smooth lips

sunscreen

SPF 20

SHINE 30

Neutrogena®

NET WT. 0.35 OZ. (10G)

PRINCIPAL DISPLAY PANEL - 10 g Tube Label, Gleam 40

LIP

SOOTHER

MOISTURE SHINE

cooling hydragel

promotes hydration

for smooth lips

sunscreen

SPF 20

GLEAM 40

Neutrogena®

NET WT. 0.35 OZ. (10G)

PRINCIPAL DISPLAY PANEL - 10 g Tube Label, Glaze 60

LIP

SOOTHER

MOISTURE SHINE

cooling hydragel

promotes hydration

for smooth lips

sunscreen

SPF 20

GLAZE 60

Neutrogena®

NET WT. 0.35 OZ. (10G)

PRINCIPAL DISPLAY PANEL - 10 g Tube Label, Glow 70

LIP

SOOTHER

MOISTURE SHINE

cooling hydragel

promotes hydration

for smooth lips

sunscreen

SPF 20

GLOW 70

Neutrogena®

NET WT. 0.35 OZ. (10G)